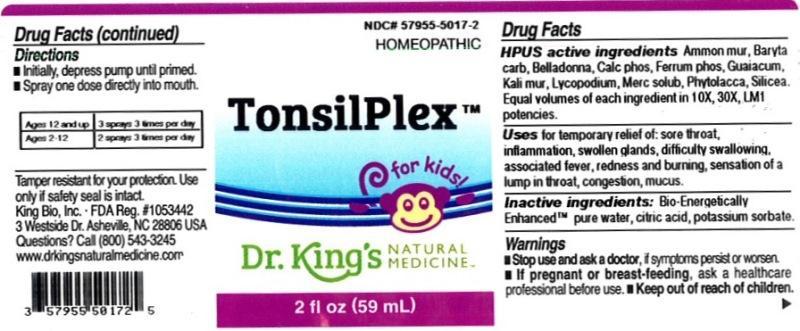 DRUG LABEL: TonsilPlex
NDC: 57955-5017 | Form: LIQUID
Manufacturer: King Bio Inc.
Category: homeopathic | Type: HUMAN OTC DRUG LABEL
Date: 20151029

ACTIVE INGREDIENTS: AMMONIUM CHLORIDE 10 [hp_X]/59 mL; BARIUM CARBONATE 10 [hp_X]/59 mL; ATROPA BELLADONNA 10 [hp_X]/59 mL; TRIBASIC CALCIUM PHOSPHATE 10 [hp_X]/59 mL; FERROSOFERRIC PHOSPHATE 10 [hp_X]/59 mL; GUAIACUM OFFICINALE RESIN 10 [hp_X]/59 mL; POTASSIUM CHLORIDE 10 [hp_X]/59 mL; LYCOPODIUM CLAVATUM SPORE 10 [hp_X]/59 mL; MERCURIUS SOLUBILIS 10 [hp_X]/59 mL; PHYTOLACCA AMERICANA ROOT 10 [hp_X]/59 mL; SILICON DIOXIDE 10 [hp_X]/59 mL
INACTIVE INGREDIENTS: WATER; ANHYDROUS CITRIC ACID; POTASSIUM SORBATE

TonsilPlex

ACTIVE INGREDIENT

Drug Facts__________________________________________________________________________________________________________

HPUS active ingredients: Ammonium muriaticum, Baryta carbonica, Belladonna, Calcarea phosphorica, Ferrum phosphoricum, Guaiacum, Kali muriaticum, Lycopodium clavatum, Mercurius solubilis, Phytolacca decandra, Silicea. Equal volumes of each ingredient in 10X, 30X, LM1 potencies.

INDICATIONS AND USAGE

Uses for temporary relief of: sore throat, inflammation, swollen glands, difficulty swallowing, associated fever, redness and burning, sensation of a lump in throat, congestion, mucus.

Inactive Ingredients:

Bio-Energetically Enhanced™ pure water, citric acid and potassium sorbate.

Warnings

- Stop use and ask your doctor if symptoms persist or worsen.
- If pregnant or breast-feeding, ask a healthcare professional before use.

- Keep out of reach of children.

Directions

- Initially, depress pump until primed.
- Spray one dose directly into mouth.
- Adults 12 and up: 3 sprays 3 times per day.
- Ages 2-12: 2 sprays 3 times per day.

OTHER SAFETY INFORMATION

Tamper resistant for your protection. Use only if seal is intact.

PURPOSE

Uses for temporary relief of:

- sore throat
- inflammation
- swollen glands
- difficulty swallowing
- associated fever
- redness and burning
- sensation of a lump in throat
- congestion
- mucus